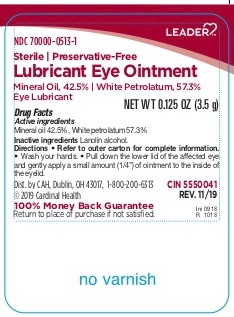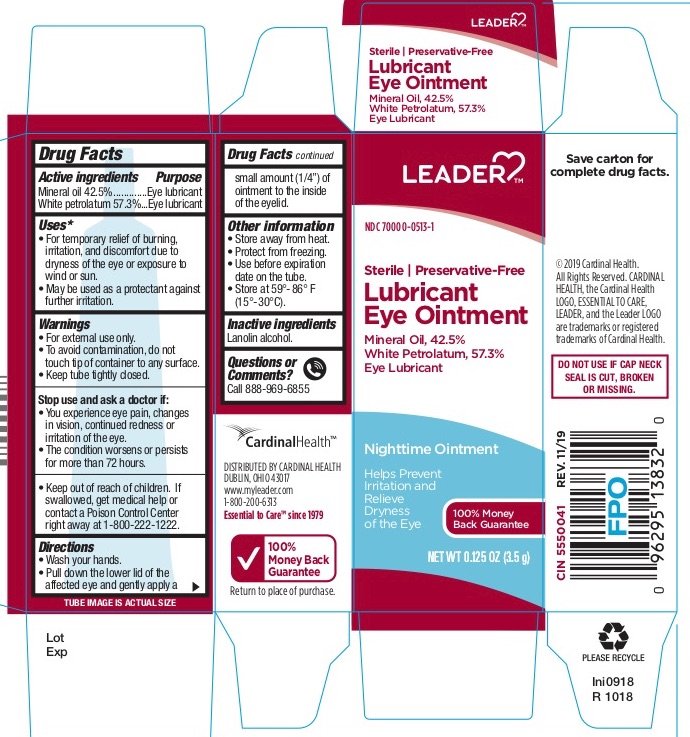 DRUG LABEL: Leader Lubricant Eye
NDC: 70000-0513 | Form: OINTMENT
Manufacturer: Leader
Category: otc | Type: HUMAN OTC DRUG LABEL
Date: 20250718

ACTIVE INGREDIENTS: MINERAL OIL 425 mg/1 g; PETROLATUM 573 mg/1 g
INACTIVE INGREDIENTS: LANOLIN ALCOHOLS

Leader Lubricant Eye Ointment

Active ingredients Purpose

Mineral oil 42.5%........................................................ Eye Lubricant

White petrolatum 57.3%............................................. Eye Lubricant

Uses

- For the temporary relief of burning, irritation, and discomfort due to dryness or the eye or exposure to wind or sun.
- May be used as a protectant against further irritation

Warnings

- For external use only.
- To avoid contamination, do not touch tip of container to any surface.
- Keep tube tightly closed.

Stop use and ask a doctor if:

- You experience eye pain, changes in vision, continued redness or irritation of the eye.
- The condition worsens or persists for more than 72 hours. .

Keep out of reach of children.

If swallowed, get medical help or contact a Poison Control Center right away at 1-800-222-1222.

Directions

• Wash your hands.
• Pull down the lower lid of the affected eye and gently apply a small amount (1/4”) of ointment to the inside of the eyelid.

Other information

- store away from heat
- protect from freezing
- use before expiration date on the tube
- store at 59°-86° (15°-30°)

Inactive ingredient

lanolin alcohol

Directions

• Wash your hands.
• Pull down the lower lid of the affected eye and gently apply a small amount (1/4”) of ointment to the inside of the eyelid.

PACKAGE LABEL

Leader Lubricant Eye Ointment

Principal Display Panel